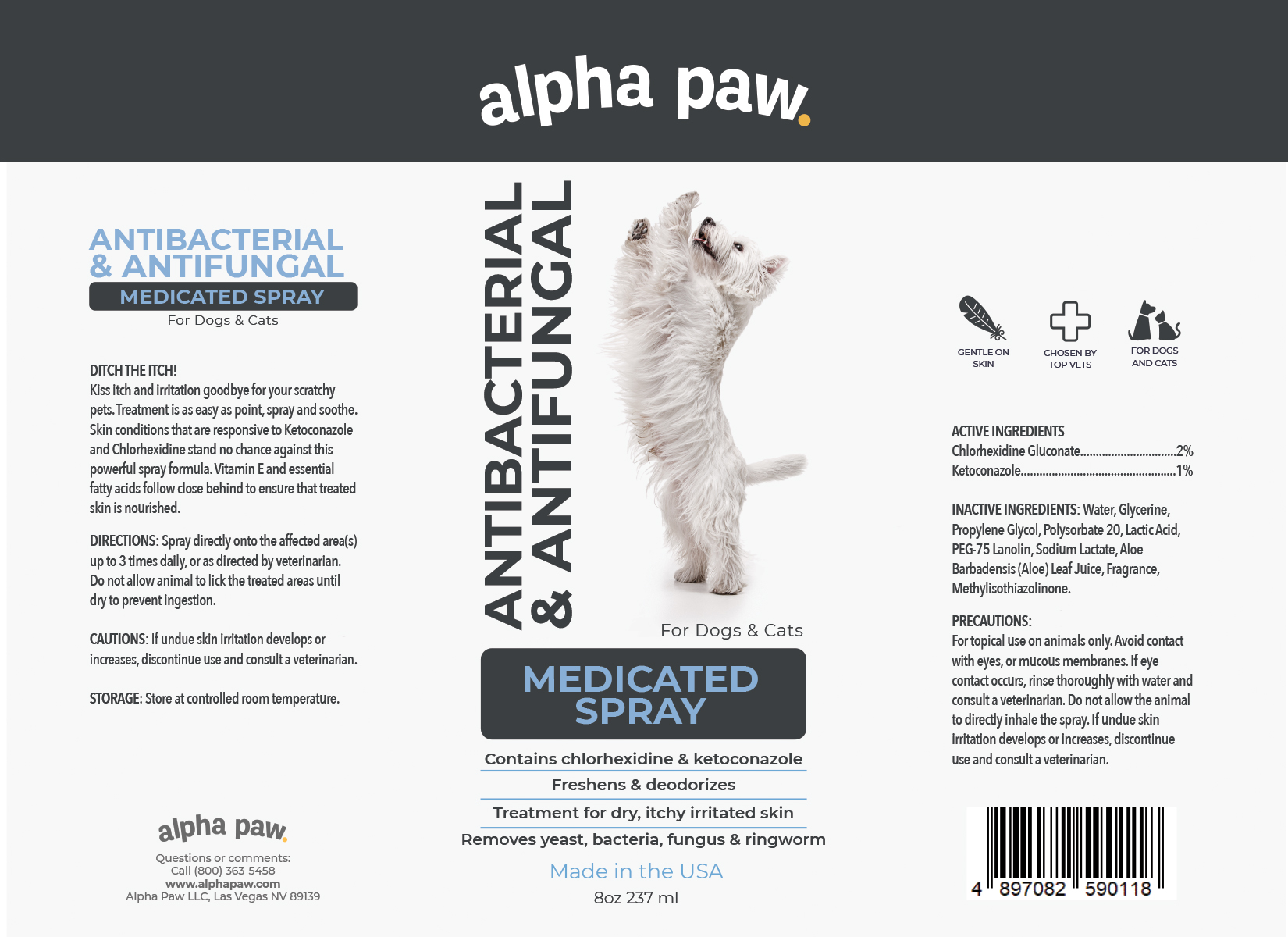 DRUG LABEL: ANTIBACTERIAL ANTIFUNGAL MEDICATED
NDC: 86175-003 | Form: SPRAY
Manufacturer: Alpha Paw Inc
Category: animal | Type: OTC ANIMAL DRUG LABEL
Date: 20230315

ACTIVE INGREDIENTS: CHLORHEXIDINE GLUCONATE 2 g/100 mL; KETOCONAZOLE 1 g/100 mL
INACTIVE INGREDIENTS: WATER; GLYCERIN; PROPYLENE GLYCOL; POLYSORBATE 20; LACTIC ACID, UNSPECIFIED FORM; PEG-75 LANOLIN; SODIUM LACTATE; ALOE VERA LEAF; METHYLISOTHIAZOLINONE

ANTIBACTERIAL & ANTIFUNGAL MEDICATED SPRAY

ACTIVE INGREDIENTS

Chlorhexidine Gluconate...............................2%
Ketoconazole..................................................1%

PURPOSE

ANTIBACTERIAL & ANTIFUNGAL MEDICATED SPRAY For Dogs & Cats

DITCH THE ITCH!

Kiss itch and irritation goodbye for your scratchy pets. Treatment is as easy as point, spray and soothe. Skin conditions that are responsive to Ketoconazole and Chlorhexidine stand no chance against this powerful spray formula. Vitamin E and essential fatty acids follow close behind to ensure that treated skin is nourished.

INACTIVE INGREDIENTS

Water, Glycerine, Propylene Glycol, Polysorbate 20, Lactic Acid, PEG-75 Lanolin, Sodium Lactate, Aloe Barbadensis (Aloe) Leaf Juice, Fragrance, Methylisothiazolinone.

PRECAUTIONS

For topical use on animals only. Avoid contact with eyes, or mucous membranes. If eye contact occurs, rinse thoroughly with water and consult a veterinarian. Do not allow the animal to directly inhale the spray. If undue skin irritation develops or increases, discontinue use and consult a veterinarian

DIRECTIONS

Spray directly onto the affected area(s) up to 3 times daily, or as directed by veterinarian. Do not allow animal to lick the treated areas until
dry to prevent ingestion.

CAUTIONS

If undue skin irritation develops or increases, discontinue use and consult a veterinarian.

STORAGE

Store at controlled room temperature.

Contains chlorhexidine & ketoconazole
Freshens & deodorizes
Treatment for dry, itchy irritated skin
Removes yeast, bacteria, fungus & ringworm

GENTLE ON SKIN
CHOSEN BY TOP VETS
FOR DOGS AND CATS

ALPHA PAW
Questions or Comments:
Call (800) 363-5458
www.alphapaw.com
Alpha Paw LLC, Las Vegas NV 89139

Packaging

Package 237mL